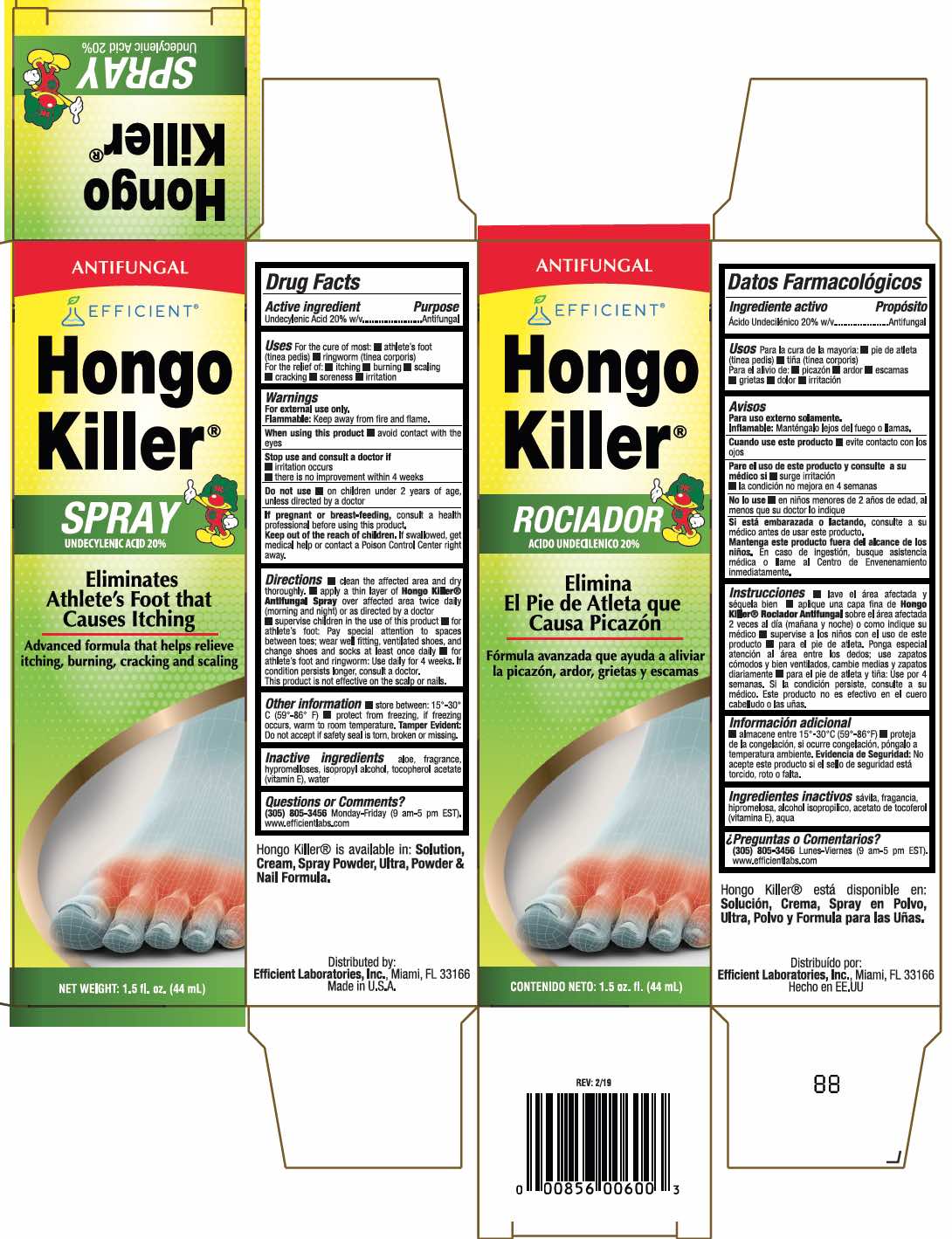 DRUG LABEL: Hongo Killer
NDC: 58593-601 | Form: SPRAY
Manufacturer: Efficient Laboratories Inc
Category: otc | Type: HUMAN OTC DRUG LABEL
Date: 20251014

ACTIVE INGREDIENTS: UNDECYLENIC ACID 2 mg/10 mL
INACTIVE INGREDIENTS: HYPROMELLOSE 2208 (100 MPA.S); ALOE VERA LEAF; ISOPROPYL ALCOHOL; .ALPHA.-TOCOPHEROL; WATER

Drug Facts

Active Ingredient Purpose

Undecylenic Acid 20% w/v.......... Antifungal

Purpose: Antifungal

INDICATIONS AND USAGE

Uses For the cure of most:

- athlete's foot (tinea pedis)
- ringworm (tinea corporis)

For the relief of:

- itching
- burning
- scaling
- cracking
- soreness
- irritation

WARNINGS

For external use only.

Flammable: Keep away from fire and flame

When using this product

- avoid contact with the eyes and mucous membrane.

Stop use and consult a doctor if

- irritation occurs
- there is no improvement within 4 weeks

Do not use

- on children under 2 years of age unless directed by a doctor.

PREGNANCY OR BREAST FEEDING

If pregnant or breast-feeding, consult a health professional before using this product.

KEEP OUT OF REACH OF CHILDREN

Keep out of the reach of children. If swallowed, get medical help or contact a Poison Control Center right away.

Directions

- Clean the affected area and dry thoroughly.
- Apply a thin layer of Hongo Killer Antifungal Spray over affected area twice daily (morning and night) or as directed by a doctor.
- Supervise children in the use of this product
- For athlete's foot: Pay special attention to spaces between toes; wear well fitting, ventilated shoes, and change shoes and socks at least once daily.
- For athlete's foot and ringworm, use daily for 4 weeks. If condition persists longer, consult a doctor. This product is not effective on the scalp and nails.

INACTIVE INGREDIENT

Inactive ingredients aloe vera, fragrance, hypromelloses, isopropyl alcohol, tocopherol acetate (vitamin E), water

Questions or Comments?

(305) 805-3456 Monday-Friday (9 am - 5 pm EST).

www.efficientlabs.com